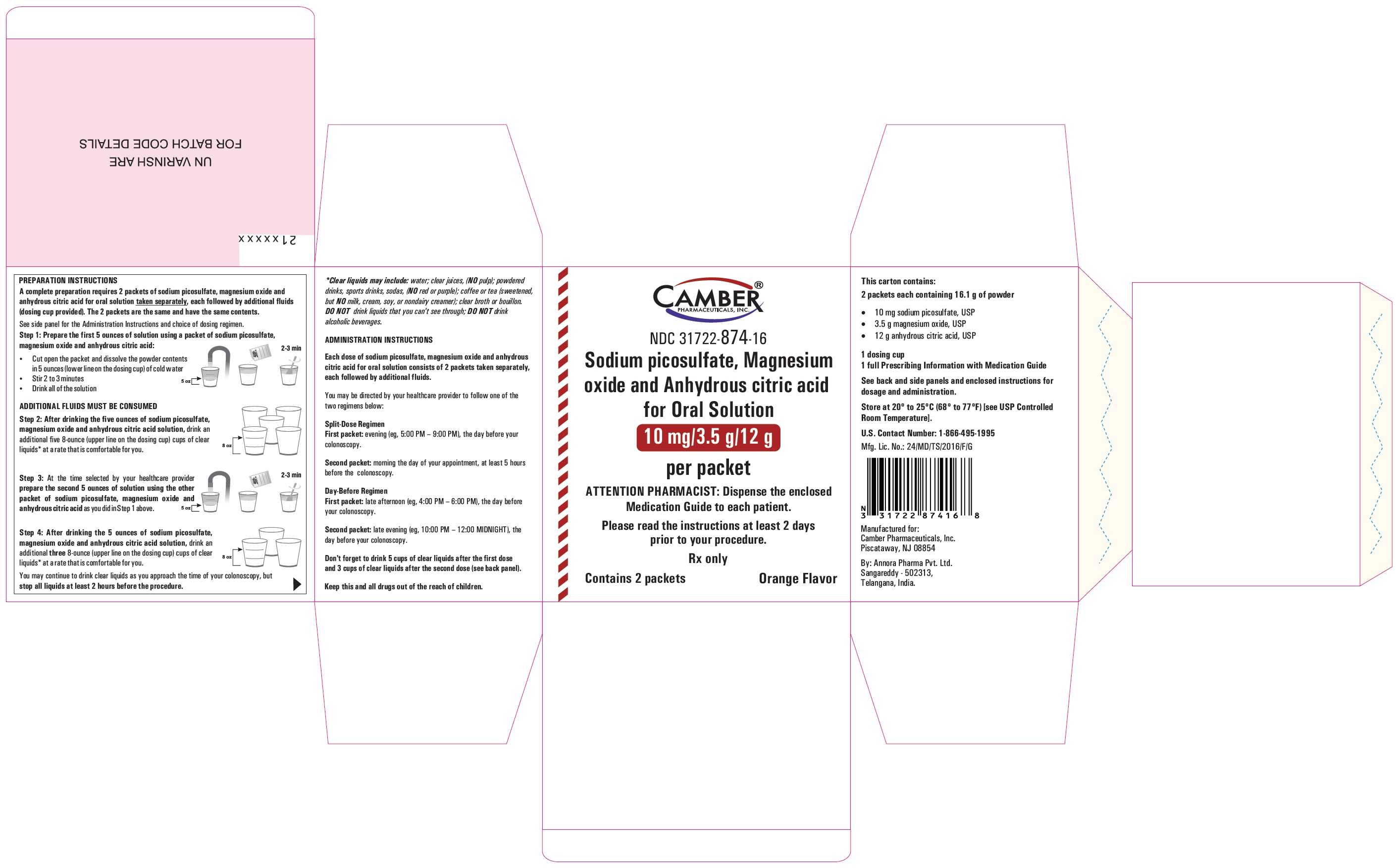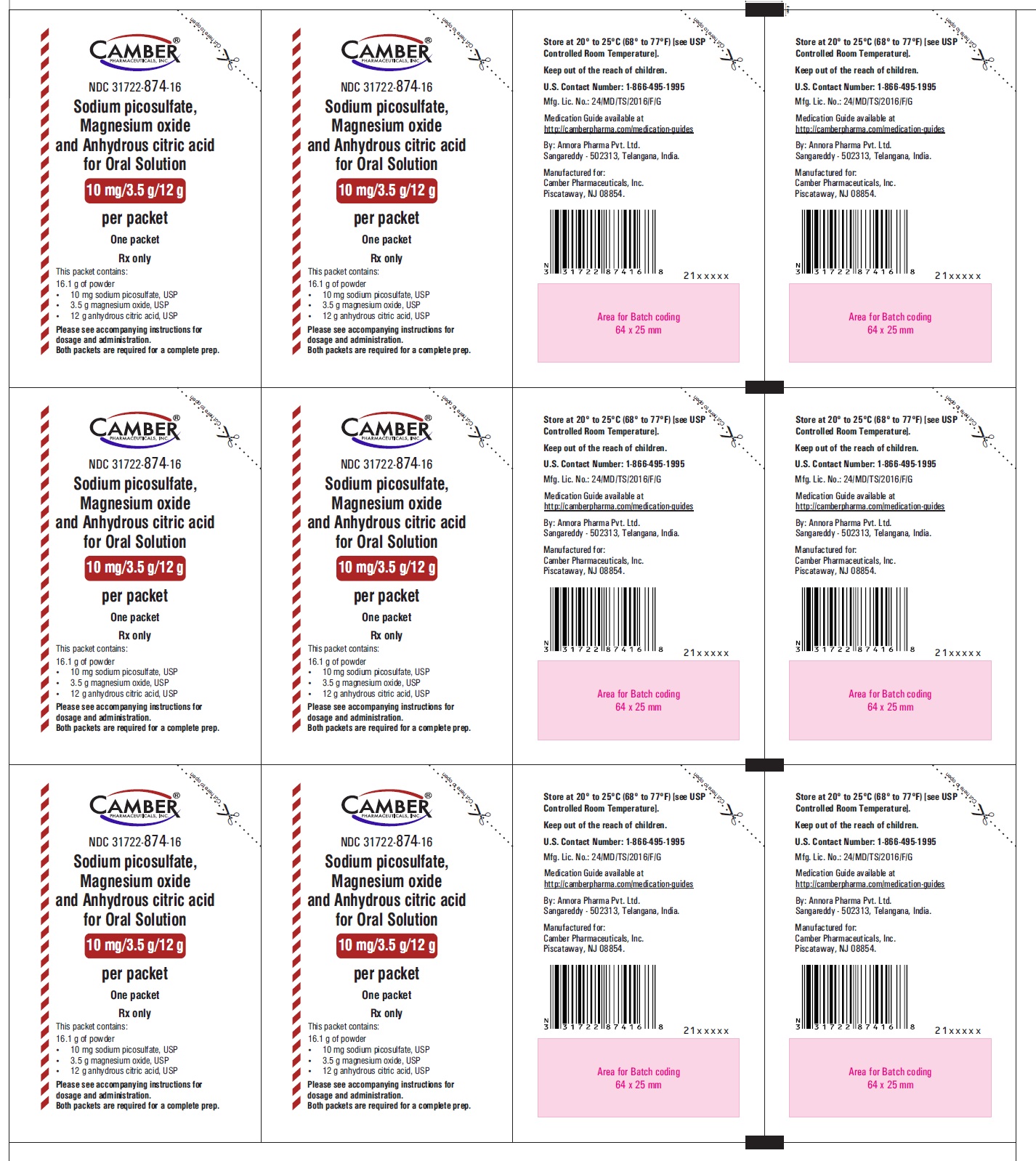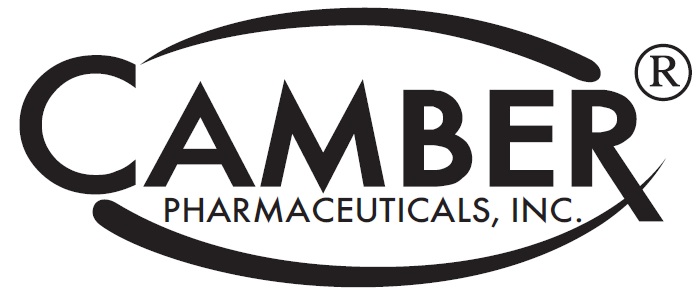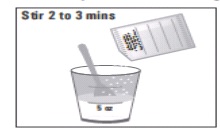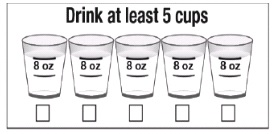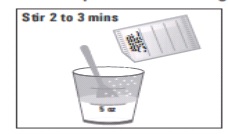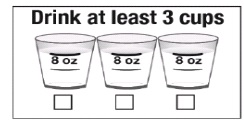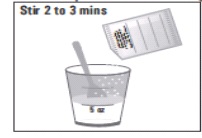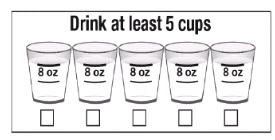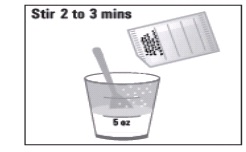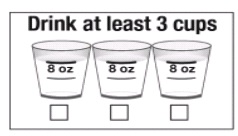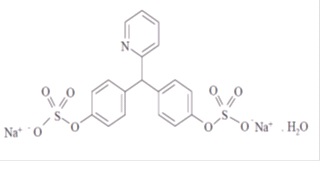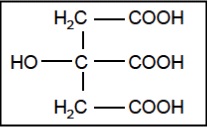 DRUG LABEL: SODIUM PICOSULFATE, MAGNESIUM OXIDE AND ANHYDROUS CITRIC ACID

NDC: 31722-874 | Form: POWDER, METERED
Manufacturer: Camber Pharmaceuticals, Inc.
Category: prescription | Type: HUMAN PRESCRIPTION DRUG LABEL
Date: 20220811

ACTIVE INGREDIENTS: SODIUM PICOSULFATE 10 mg/16.1 g; MAGNESIUM OXIDE 3.5 g/16.1 g; ANHYDROUS CITRIC ACID 12 g/16.1 g
INACTIVE INGREDIENTS: GLYCERYL DIBEHENATE; POTASSIUM BICARBONATE; SACCHARIN SODIUM; MALTODEXTRIN; .ALPHA.-TOCOPHEROL, DL-

HIGHLIGHTS OF PRESCRIBING INFORMATION

These highlights do not include all the information needed to use SODIUM PICOSULFATE, MAGNESIUM OXIDE AND ANHYDROUS CITRIC ACID FOR ORAL SOLUTION safely and effectively. See full prescribing information for SODIUM PICOSULFATE, MAGNESIUM OXIDE AND ANHYDROUS CITRIC ACID FOR ORAL SOLUTION.
SODIUM PICOSULFATE, MAGNESIUM OXIDE AND ANHYDROUS CITRIC ACID for oral solution
Initial U.S. Approval: 2012

1 INDICATIONS AND USAGE

Sodium picosulfate, magnesium oxide and anhydrous citric acid for oral solution is a combination of sodium picosulfate, a stimulant laxative, and magnesium oxide and anhydrous citric acid which form magnesium citrate, an osmotic laxative, indicated for cleansing of the colon as a preparation for colonoscopy in adults and pediatric patients ages 9 years and older. (1)

2 DOSAGE AND ADMINISTRATION

Preparation and Administration
• Each packet of sodium picosulfate, magnesium oxide and anhydrous citric acid must be dissolved with water prior to ingestion and administered according to the dosing regimen. Direct ingestion of the undissolved powder may increase the risk of nausea, vomiting and dehydration. (2.2, 5.8)
• Two doses (one packet per dose) of sodium picosulfate, magnesium oxide and anhydrous citric acid for oral solution are required for a complete preparation for colonoscopy. The preferred method is the “Split-Dose” method. The alternative is the “Day Before” method. (2.1)
• Additional fluids must be consumed after every dose of sodium picosulfate, magnesium oxide and anhydrous citric acid for oral solution in both dosing regimens. (2.1, 5.1)
• Do not take oral medications within 1 hour of start of each dose. (2.1, 7.2)
• If taking tetracycline or fluoroquinolone antibiotics, iron, digoxin, chlorpromazine, or penicillamine, take these medications at least 2 hours before and not less than 6 hours after administration of sodium picosulfate, magnesium oxide and anhydrous citric acid for oral solution. (2.1, 7.3)
• For complete information on preparation before colonoscopy and administration of the dosage regimen, see full prescribing information. (2.1, 2.2, 2.3)
Split-Dose Dosage Regimen (Preferred Method) (2.2)
• First dose: administer during evening before the colonoscopy
• Second dose: administer the next day, during the morning prior to the colonoscopy.
Day-Before Dosage Regimen (Alternative Method), if Split-Dosing is inappropriate (2.3)
• First dose: administer during afternoon or early evening before the colonoscopy.
• Second dose: administer 6 hours later during evening before colonoscopy.

3 DOSAGE FORMS AND STRENGTHS

For oral solution: Each of 2 packets contains 16.1 g of powder for orange flavor: 10 mg sodium picosulfate, 3.5 g magnesium oxide and 12 g anhydrous citric acid (3)

4 CONTRAINDICATIONS

• Severe renal impairment (creatinine clearance less than 30 mL/minute) (4)
• Gastrointestinal (GI) obstruction or ileus (4)
• Bowel perforation (4)
• Toxic colitis or toxic megacolon (4)
• Gastric retention (4)
• Hypersensitivity to any of the ingredients (4)

5 WARNINGS AND PRECAUTIONS

• Risk of fluid and electrolyte abnormalities: Encourage adequate hydration, assess concurrent medications, and consider laboratory assessments prior to and after use. (5.1, 5.2, 7.1)
• Cardiac arrhythmias: Consider pre-dose and post-colonoscopy ECGs in patients at increased risk. (5.2)
• Seizures: Use caution in patients with a history of seizures and patients at increased risk of seizure, including medications that lower the seizure threshold. (5.3, 7.1)
• Patients with mild to moderate renal impairment or taking concomitant medications that affect renal function: Use caution, ensure adequate hydration and consider testing. (4, 5.4, 7.1)
• Mucosal ulcerations: Consider potential for mucosal ulcerations when interpreting colonoscopy findings in patients with known or suspected inflammatory bowel disease. (5.5)
• Suspected GI obstruction or perforation: Rule out diagnosis before administration. (4, 5.6)
• Patients at risk for aspiration: Observe during administration. (5.7)
• Risk of vomiting and other GI complications with ingestion of undissolved powder: Dissolve each packet in 5 ounces of cold water and administered at separate times according to the dosing regimen. (2.3, 2.4, 5.8)

6 ADVERSE REACTIONS

Most common adverse reactions are:
• Adults (>1%): nausea, headache and vomiting. (6.1)
• Pediatrics 9 to 16 years (>5%): nausea, vomiting, and abdominal pain. (6.1)
To report SUSPECTED ADVERSE REACTIONS, contact Annora Pharma Private Limited at 1-866-495-1995 or FDA at 1-800-FDA-1088 or www.fda.gov/medwatch.

7 DRUG INTERACTIONS

Drugs that increase risks due to fluid and electrolyte changes. (7.1)

FULL PRESCRIBING INFORMATION

1 INDICATIONS AND USAGE

Sodium picosulfate, magnesium oxide and anhydrous citric acid for oral solution is indicated for cleansing of the colon as a preparation for colonoscopy in adults and pediatric patients 9 years of age and older.

2 DOSAGE AND ADMINISTRATION

2.1 Important Preparation and Administration Instructions

• Correct fluid and electrolyte abnormalities before administration of sodium picosulfate, magnesium oxide and anhydrous citric acid for oral solution [see Warnings and Precautions (5.1)].
• Two doses (one packet per dose) of sodium picosulfate, magnesium oxide and anhydrous citric acid for oral solution are required for a complete preparation for colonoscopy either as a Split-Dose (preferred) or Day-Before dosing regimen.
• The preferred method is the “Split-Dose” method and consists of two separate doses: the first dose during the evening before the colonoscopy and the second dose the next day, the morning of the day of the colonoscopy [see Dosage and Administration (2.2)].
• The alternative method is the “Day Before” method and consists of two separate doses: the first dose during the afternoon or early evening before the colonoscopy and the second dose 6 hours later during the evening before the colonoscopy [see Dosage and Administration (2.3)].
• Each packet of sodium picosulfate, magnesium oxide and anhydrous citric acid must be dissolved in 5 ounces of cold water prior to ingestion and administered according to the dosing regimen. Direct ingestion of the undissolved powder may increase the risk of nausea, vomiting, dehydration and electrolyte disturbances [see Warnings and Precautions (5.8)].
• Additional fluids must be consumed after every dose of sodium picosulfate, magnesium oxide and anhydrous citric acid for oral solution in both dosing regimens [see Dosage and Administration (2.2), Warnings and Precautions (5.1)].
• Consume only clear fluids (no solid food) from the start of sodium picosulfate, magnesium oxide and anhydrous citric acid for oral solution treatment until after the colonoscopy.
• Do not eat solid food or dairy and do not drink anything colored red or purple.
• Do not drink alcohol.
• Do not take other laxatives while taking sodium picosulfate, magnesium oxide and anhydrous citric acid for oral solution.
• Do not take oral medications within one hour before or after starting sodium picosulfate, magnesium oxide and anhydrous citric acid for oral solution.
• If taking tetracycline or fluoroquinolone antibiotics, iron, digoxin, chlorpromazine, or penicillamine, take these medications at least 2 hours before and not less than 6 hours after administration of sodium picosulfate, magnesium oxide and anhydrous citric acid for oral solution [see Drug Interactions (7.2)].

• Stop consumption of all fluids at least 2 hours before the colonoscopy.

2.2 Reconstitution of Sodium Picosulfate, Magnesium Oxide and Anhydrous Citric Acid Powder

1. Reconstitute the sodium picosulfate, magnesium oxide and anhydrous citric acid powder immediately before each administration. Do not prepare the solution in advance.
2. Fill the supplied dosing cup with cold water up to the lower (5-ounce) line on the cup and pour in the contents of one packet of sodium picosulfate, magnesium oxide and anhydrous citric acid powder.
3. Stir for 2 to 3 minutes. The reconstituted sodium picosulfate, magnesium oxide and anhydrous citric acid solution may become slightly warm as the powder dissolves.

2.3 Split-Dose Dosing Regimen (Preferred Method)

The Split-Dose regimen is the preferred dosing method. The recommended dosage in adults and pediatric patients 9 years of age and older is shown below. Instruct patients to take two separate doses (one packet per dose) in conjunction with fluids.
Dose 1 – On the day before colonoscopy:
• Instruct patients to consume only clear liquids (no solid food or dairy) on the day before the colonoscopy up until 2 hours before the time of the colonoscopy.
• Take the first dose of sodium picosulfate, magnesium oxide and anhydrous citric acid for oral solution during the evening before the colonoscopy (e.g., 5:00 to 9:00 PM).
• Follow sodium picosulfate, magnesium oxide and anhydrous citric acid for oral solution by drinking at least five 8-ounce cups of clear liquids (40 ounces total), using the upper line on the cup, within 5 hours and before bed.
• If severe bloating, distention, or abdominal pain occurs, following the first dose, delay the second dose until the symptoms resolve.
Dose 2 – Next morning on the day of colonoscopy (start approximately 5 hours prior to colonoscopy):
• Continue to consume only clear liquids (no solid food or dairy).
• Take the second dose of sodium picosulfate, magnesium oxide and anhydrous citric acid for oral solution.
• Following the sodium picosulfate, magnesium oxide and anhydrous citric acid for oral solution dose, drink at least three 8-ounce cups of clear liquids (24 ounces), using the upper line on the cup, at least 2 hours before the colonoscopy.

2.4 Day-Before Dosing Regimen (Alternative Method)

The Day-Before regimen is the alternative dosing method for patients for whom the Split-Dosing is inappropriate. The recommended dosage in adults and pediatric patients 9 years of age and older is shown below. Instruct patients to take two separate doses (one packet per dose) in conjunction with fluids
Dose 1 – On the day before colonoscopy:
• Instruct patients to consume only clear liquids (no solid food or dairy) on the day before the colonoscopy up until 2 hours before the time of the colonoscopy.
• Take the first dose of sodium picosulfate, magnesium oxide and anhydrous citric acid for oral solution in the afternoon or early evening before the colonoscopy (e.g., 4:00 to 6:00 PM).
• Following the sodium picosulfate, magnesium oxide and anhydrous citric acid for oral solution dose, drink at least five 8-ounce cups of clear liquids (40 ounces total), using the upper line on the cup, within 5 hours and before the next dose.
• If severe bloating, distention, or abdominal pain occurs, following the first dose, delay the second dose until the symptoms resolve.
Dose 2 – Approximately 6 hours later in the evening the night before the colonoscopy (e.g., 10:00 PM to 12:00 AM):
• Take the second dose of sodium picosulfate, magnesium oxide and anhydrous citric acid for oral solution.
• Following the sodium picosulfate, magnesium oxide and anhydrous citric acid for oral solution dose, drink at least three 8-ounce cups (24 ounces), using the upper line on the cup, of clear liquids within 5 hours and before bed.
Storage
Reconstitute immediately before use. Do not prepare the solution in advance or store the solution for later use. Do not refrigerate or add ice to the solution.

3 DOSAGE FORMS AND STRENGTHS

For oral solution: Each of the two packets contains 10 mg of sodium picosulfate, 3.5 g of magnesium oxide and 12 g of anhydrous citric acid in 16.1g of powder for orange flavor.

4 CONTRAINDICATIONS

Sodium picosulfate, magnesium oxide and anhydrous citric acid for oral solution is contraindicated in the following conditions:
• Patients with severe renal impairment (creatinine clearance less than 30 mL/minute) which may result in accumulation of magnesium [see Warnings and Precautions (5.4)]
• Gastrointestinal obstruction or ileus [see Warnings and Precautions (5.6)]
• Bowel perforation [see Warnings and Precautions (5.6)]
• Toxic colitis or toxic megacolon
• Gastric retention
• Hypersensitivity to any of the ingredients in sodium picosulfate, magnesium oxide and anhydrous citric acid for oral solution [see Adverse Reactions (6.2)]

5 WARNINGS AND PRECAUTIONS

5.1 Serious Fluid and Electrolyte Abnormalities

Advise patients to hydrate adequately before, during, and after the use of sodium picosulfate, magnesium oxide and anhydrous citric acid. Use caution in patients with congestive heart failure when replacing fluids. If a patient develops significant vomiting or signs of dehydration including signs of orthostatic hypotension after taking sodium picosulfate, magnesium oxide and anhydrous citric acid, consider performing post-colonoscopy lab tests (electrolytes, creatinine, and BUN) and treat accordingly. Approximately 20% of adult patients in both arms (sodium picosulfate, magnesium oxide and anhydrous citric acid, 2L of PEG + E plus two x 5 mg bisacodyl tablets) of clinical trials of sodium picosulfate, magnesium oxide and anhydrous citric acid had orthostatic changes (changes in blood pressure and/or heart rate) on the day of colonoscopy. In adult clinical trials orthostatic changes were documented up to seven days post colonoscopy. In a single study of patients 9 to 16 years of age, approximately 20% of patients in sodium picosulfate, magnesium oxide and anhydrous citric acid arms had orthostatic changes (changes in blood pressure and/or heart rate) compared with approximately 7% of those who received the comparator (PEG) [see Clinical Studies (14)]. These changes occurred up to five days post colonoscopy.
Fluid and electrolyte disturbances can lead to serious adverse reactions including cardiac arrhythmias or seizures and renal impairment. Correct fluid and electrolyte abnormalities before treatment with sodium picosulfate, magnesium oxide and anhydrous citric acid [see Dosage and Administration (2.1)] . In addition, use caution when prescribing sodium picosulfate, magnesium oxide and anhydrous citric acid for patients who have conditions or who are using medications that increase the risk for fluid and electrolyte disturbances or that may increase the risk of adverse events of seizure, arrhythmia, and renal impairment [see Drug Interactions (7.1)].

5.2 Cardiac Arrhythmias

There have been rare reports of serious arrhythmias associated with the use of ionic osmotic laxative products for bowel preparation. Use caution when prescribing sodium picosulfate, magnesium oxide and anhydrous citric acid for patients at increased risk of arrhythmias (e.g., patients with a history of prolonged QT, uncontrolled arrhythmias, recent myocardial infarction, unstable angina, congestive heart failure, or cardiomyopathy). Consider pre-dose and post-colonoscopy ECGs in patients at increased risk of serious cardiac arrhythmias.

5.3 Seizures

There have been reports of generalized tonic-clonic seizures with the use of bowel preparation products in patients with no prior history of seizures. The seizure cases were associated with electrolyte abnormalities (e.g., hyponatremia, hypokalemia, hypocalcemia, and hypomagnesemia) and low serum osmolality. The neurologic abnormalities resolved with correction of fluid and electrolyte abnormalities.
Use caution when prescribing sodium picosulfate, magnesium oxide and anhydrous citric acid for patients with a history of seizures and in patients at risk of seizure, such as patients taking medications that lower the seizure threshold (e.g., tricyclic antidepressants), patients withdrawing from alcohol or benzodiazepines, or patients with known or suspected hyponatremia [see Adverse Reactions (6.2)].

5.4 Use in Patients with Renal Impairment

Sodium picosulfate, magnesium oxide and anhydrous citric acid is contraindicated in patients with severe renal impairment (creatinine clearance less than 30 mL/min), accumulation of magnesium in plasma may occur [see Contraindications (4)]. As with other magnesium containing bowel preparations, use caution when prescribing sodium picosulfate, magnesium oxide and anhydrous citric acid for patients with mild to moderate renal impairment or patients taking concomitant medications that may affect renal function (such as diuretics, angiotensin converting enzyme inhibitors, angiotensin receptor blockers, or non-steroidal anti-inflammatory drugs) [see Drug Interactions (7.1)]. These patients may be at increased risk for renal injury. Advise these patients of the importance of adequate hydration before, during and after the use of sodium picosulfate, magnesium oxide and anhydrous citric acid. Consider performing baseline and post-colonoscopy laboratory tests (electrolytes, creatinine, and BUN) in these patients.

5.5 Colonic Mucosal Ulceration, Ischemic Colitis and Ulcerative Colitis

Osmotic laxatives may produce colonic mucosal aphthous ulcerations and there have been reports of more serious cases of ischemic colitis requiring hospitalization. Concurrent use of additional stimulant laxatives with sodium picosulfate, magnesium oxide and anhydrous citric acid may increase this risk. The potential for mucosal ulcerations should be considered when interpreting colonoscopy findings in patients with known or suspected inflammatory bowel disease [see Adverse Reactions (6.2)].

5.6 Use in Patients with Significant Gastrointestinal Disease

If gastrointestinal obstruction or perforation is suspected, perform appropriate diagnostic studies to rule out these conditions before administering sodium picosulfate, magnesium oxide and anhydrous citric acid [see Contraindications (4)]. Use with caution in patients with severe active ulcerative colitis.

5.7 Aspiration

Patients with impaired gag reflex are at risk for regurgitation or aspiration during the administration of sodium picosulfate, magnesium oxide and anhydrous citric acid. Observe these patients during the administration of sodium picosulfate, magnesium oxide and anhydrous citric acid. Use with caution in these patients.

5.8 Risk of Vomiting and Other Gastrointestinal Complications with Ingestion of Undissolved Powder

Each packet must be dissolved in 5 ounces of cold water and administered at separate times according to the dosing regimen [see Dosage and Administration (2.3,2.4)] . Ingestion of additional water is important to patient tolerance. Direct ingestion of the undissolved powder may increase the risk of nausea, vomiting, dehydration, and electrolyte disturbances.

6 ADVERSE REACTIONS

The following serious or otherwise important adverse reactions for bowel preparations are described elsewhere in the labeling:
• Serious Fluid and Electrolyte Abnormalities [see Warnings and Precautions (5.1)]
• Cardiac Arrhythmias [see Warnings and Precautions (5.2)]
• Seizures [see Warnings and Precautions (5.3)]
• Use in Patients with Renal Impairment [see Warnings and Precautions (5.4)]
• Colonic Mucosal Ulceration, Ischemic Colitis and Ulcerative Colitis [see Warnings and Precautions (5.5)]
• Use in Patients with Significant Gastrointestinal Disease [see Warnings and Precautions (5.6)]
• Aspiration [see Warnings and Precautions (5.7)]
• Risk of Vomiting and Other Gastrointestinal Complications with Ingestion of Undissolved Powder [see Warnings and Precautions (5.8)]

6.1 Clinical Trials Experience

Because clinical trials are conducted under widely varying conditions, adverse reaction rates observed in the clinical trials of a drug cannot be directly compared to rates in clinical trials of another drug and may not reflect the rates observed in practice.
In randomized, multicenter, controlled clinical trials, nausea, headache, and vomiting were the most common adverse reactions (>1%) following sodium picosulfate, magnesium oxide and anhydrous citric acid administration. The patients were not blinded to the study drug. Since abdominal bloating, distension, pain/cramping, and watery diarrhea are known to occur in response to colon cleansing preparations, these effects were documented as adverse events in the clinical trials only if they required medical intervention (such as a change in study drug or led to study discontinuation, therapeutic or diagnostic procedures, met the criteria for a serious adverse event), or showed clinically significant worsening during the study that was not in the frame of the usual clinical course, as determined by the investigator.
Sodium picosulfate, magnesium oxide and anhydrous citric acid was compared for colon cleansing effectiveness with a preparation containing two liters (2L) of polyethylene glycol plus electrolytes solution (PEG + E) and two 5 mg bisacodyl tablets, all administered the day before the procedure. Table 1 displays the most common adverse reactions in Study 1 and Study 2 for the sodium picosulfate, magnesium oxide and anhydrous citric acid Split-Dose and Day-Before dosing regimens, respectively, each as compared to the comparator preparation.
Table 1: Treatment-Emergent Adverse Reactions observed in at Least (>1%) of Patients using the Split-Dose Regimen and Day-Before Regimen **

Adverse Reaction | Study 1: Split-Dose Regimen |  | Study 2: Day-Before Regimen
Adverse Reaction | Sodium picosulfate, magnesium oxide and anhydrous citric acid (N=305) n (% = n/N) | 2 L PEG+E* with 2 x 5-mg bisacodyl tablets (N=298) n (% = n/N) | Sodium picosulfate, magnesium oxide and anhydrous citric acid (N=296) n (% = n/N) | 2 L PEG+E* with 2 x 5mg bisacodyl tablets (N=302) n (% = n/N)
Nausea | 8 (2.6) | 11 (3.7) | 9 (3.0) | 13 (4.3)
Headache | 5 (1.6) | 5 (1.7) | 8 (2.7) | 5 (1.7)
Vomiting | 3 (1.0) | 10 (3.4) | 4 (1.4) | 6 (2.0)

* 2L PEG + E = two liters polyethylene glycol plus electrolytes solution.
**abdominal bloating, distension, pain/cramping, and watery diarrhea not requiring an intervention were not collected
Electrolyte Abnormalities
In general, sodium picosulfate, magnesium oxide and anhydrous citric acid was associated with numerically higher rates of abnormal electrolyte shifts on the day of colonoscopy compared to the preparation containing 2L of PEG + E plus two x 5-mg bisacodyl tablets (Table 2). These shifts were transient in nature and numerically similar between treatment arms at the Day 30 visit.
Table 2: Shifts from Normal Baseline to Outside the Normal Range at Day 7 and Day 30

Laboratory Parameter (direction of change) | Visit | Study 1: Split-Dose Regimen |  | Study 2: Day-Before Regimen
Laboratory Parameter (direction of change) | Visit | Sodium picosulfate, magnesium oxide and anhydrous citric acid | 2L PEG+E with 2x 5 mg bisacodyl tablets | Sodium picosulfate, magnesium oxide and anhydrous citric acid | 2L PEG+E with 2x 5 mg bisacodyl tablets
 |  | n/N (%) |  | n/N (%)
Potassium (low) | Day of Colonoscopy | 19/260 (7.3) | 11/268 (4.1) | 13/274 (4.7) | 13/271 (4.8)
 | 24 to 48 hours | 3/302 (1.0) | 2/294 (0.7) | 3/287 (1.0) | 5/292 (1.7)
 | Day 7 | 11/285 (3.9) | 8/279 (2.9) | 6/276 (2.2) | 14/278 (5.0)
 | Day 30 | 11/284 (3.9) | 8/278 (2.9) | 7/275 (2.5) | 8/284 (2.8)
Sodium (low) | Day of Colonoscopy | 11/298 (3.7) | 3/295 (1.0) | 3/286 (1.0) | 3/295 (1.0)
 | 24 to 48 hours | 1/303 (0.3) | 1/295 (0.3) | 1/288 (0.3) | 1/293 (0.3)
 | Day 7 | 2/300 (0.7) | 1/292 (0.3) | 1/285 (0.4) | 1/291 (0.3)
 | Day 30 | 2/299 (0.7) | 3/291 (1.0) | 1/284 (0.4) | 1/296 (0.3)
Chloride (low) | Day of Colonoscopy | 11/301 (3.7) | 1/298 (0.3) | 3/287 (1.0) | 0/297 (0.0)
 | 24 to 48 hours | 1/303 (0.3) | 0/295 (0.0) | 2/288 (0.7) | 0/293 (0.0)
 | Day 7 | 1/303 (0.3) | 3/295 (1.0) | 0/285 (0.0) | 0/293 (0.0)
 | Day 30 | 2/302 (0.7) | 3/294 (1.0) | 0/285 (0.0) | 0/298 (0.0)
Magnesium (high) | Day of Colonoscopy | 34/294 (11.6) | 0/294 (0.0) | 25/288 (8.7) | 1/289 (0.3)
 | 24 to 48 hours | 0/303 (0.0) | 0/295 (0.0) | 0/288 (0.0) | 0/293 (0.0)
 | Day 7 | 0/297 (0.0) | 1/291 (0.3) | 1/286 (0.3) | 1/285 (0.4)
 | Day 30 | 1/296 (0.3) | 2/290 (0.7) | 0/286 (0.0) | 0/290 (0.0)
Calcium (low) | Day of Colonoscopy | 2/292 (0.7) | 1/286 (0.3) | 0/276 (0.0) | 2/282 (0.7)
 | 24 to 48 hours | 0/303 (0.0) | 0/295 (0.0) | 0/288 (0.0) | 0/293 (0.0)
 | Day 7 | 0/293 (0.0) | 1/283 (0.4) | 0/274 (0.0) | 0/278 (0.0)
 | Day 30 | 0/292 (0.0) | 1/282 (0.4) | 0/274 (0.0) | 1/283 (0.4)
Creatinine (high) | Day of Colonoscopy | 5/260 (1.9) | 13/268 (4.9) | 12/266 (4.5) | 16/270 (5.9)
 | 24 to 48 hours | 1/303 (0.3) | 0/295 (0.0) | 0/288 (0.0) | 0/293 (0.0)
 | Day 7 | 10/264 (0.4) | 13/267 (4.8) | 10/264 (3.8) | 10/265 (3.8)
 | Day 30 | 11/264 (4.2) | 14/265 (5.3) | 18/264 (6.8) | 10/272 (3.7)
eGFR (low) | Day of Colonoscopy | 22/221 (10.0) | 17/214 (7.9) | 26/199 (13.1) | 25/224 (11.2)
 | 24 to 48 hours | 76/303 (25.1) | 72/295 (24.4) | 82/288 (28.5) | 62/293 (21.2)
 | Day 7 | 22/223 (10.0) | 17/213 (8.0) | 11/198 (5.6) | 28/219 (12.8)
 | Day 30 | 24/223 (10.8) | 21/211 (10.0) | 21/199 (10.6) | 24/224 (10.7)

Pediatrics
In the pediatric patients aged 9 to 16 years who received sodium picosulfate, magnesium oxide and anhydrous citric acid, the most common adverse reactions (> 5%) were nausea, vomiting, and abdominal pain [see Clinical Trials (14)]. Electrolytes abnormalities were observed in pediatric patients similar to those seen in adults. Three patients had abnormally low glucose levels (40 to 47 mg/dL). Two patients received sodium picosulfate, magnesium oxide and anhydrous citric acid and one received the comparator (PEG). The abnormal values occurred at the colonoscopy visit for one patient (sodium picosulfate, magnesium oxide and anhydrous citric acid) and at the 5-day follow up visit for the other two patients (sodium picosulfate, magnesium oxide and anhydrous citric acid and PEG). All three patients were asymptomatic.

6.2 Postmarketing Experience

The following adverse reactions have been identified during post approval use of other oral formulations of sodium picosulfate, magnesium oxide and anhydrous citric acid similar to sodium picosulfate, magnesium oxide and anhydrous citric acid for oral solution. Because these reactions are reported voluntarily from a population of uncertain size, it is not always possible to reliably estimate their frequency or establish a causal relationship to drug exposure.
Hypersensitivity: rash, urticaria, purpura, and anaphylaxis [see Contraindications (4)]
Gastrointestinal: abdominal pain, diarrhea, fecal incontinence, aphthoid ileal ulcers, ischemic colitis [see Warnings and Precautions (5.5)]
Neurologic: generalized tonic-clonic seizures with and without hyponatremia in epileptic patients [see Warnings and Precautions (5.3)].

7 DRUG INTERACTIONS

7.1 Drugs That May Increase Risks of Fluid and Electrolyte Abnormalities

Use caution when prescribing sodium picosulfate, magnesium oxide and anhydrous citric acid for patients with conditions and/or who are taking other drugs that increase the risk for fluid and electrolyte disturbances or may increase the risk of renal impairment, seizures, arrhythmias, or QT prolongation in the setting of fluid and electrolyte abnormalities [see Warnings and Precautions (5.1, 5.2, 5.3, 5.4)].

7.2 Potential for Reduced Drug Absorption

Sodium picosulfate, magnesium oxide and anhydrous citric acid can reduce the absorption of other co-administered drugs [see Dosage and Administration (2.1)]:
• Administer oral medications at least one hour before of the start of administration of sodium picosulfate, magnesium oxide and anhydrous citric acid.
• Administer tetracycline and fluoroquinolone antibiotics [see Drug Interactions (7.3)], iron, digoxin, chlorpromazine, and penicillamine at least 2 hours before and not less than 6 hours after administration of sodium picosulfate, magnesium oxide and anhydrous citric acid.

7.3 Antibiotics

Prior or concomitant use of antibiotics with sodium picosulfate, magnesium oxide and anhydrous citric acid for oral solution may reduce efficacy of sodium picosulfate, magnesium oxide and anhydrous citric acid as conversion of sodium picosulfate to its active metabolite BHPM is mediated by colonic bacteria.

8 USE IN SPECIFIC POPULATIONS

8.1 Pregnancy

Risk Summary
There are no data with sodium picosulfate, magnesium oxide and anhydrous citric acid use in pregnant women to determine a drug-associated risk of major birth defects, miscarriage, or adverse maternal or fetal outcomes. In an animal reproduction study, no adverse developmental effects were observed in pregnant rats when sodium picosulfate, magnesium oxide, and anhydrous citric acid were administered orally at doses 1.2 times the recommended human dose based on body surface area during organogenesis.
The estimated background risk of major birth defects and miscarriage for the indicated population is unknown. All pregnancies have a background risk of birth defect, loss, or other adverse outcomes. In the U.S. general population, the estimated background risk of major birth defects and miscarriage in clinically recognized pregnancies is 2 to 4% and 15 to 20%, respectively.
Data
Animal Data
A reproduction study with sodium picosulfate, magnesium oxide and anhydrous citric acid has been performed in pregnant rats following oral administration of up to 2,000 mg/kg twice daily (about 1.2 times the recommended human dose based on body surface area) during the period of organogenesis. There was no evidence of harm to the fetus due to sodium picosulfate, magnesium oxide and anhydrous citric acid. A reproduction study in rabbits was not adequate, as treatment-related mortalities were observed at all doses. A pre and postnatal development study with sodium picosulfate, magnesium oxide and anhydrous citric acid in rats showed no evidence of any adverse effect on pre and postnatal development at oral doses up to 2,000 mg/kg twice daily (about 1.2 times the recommended human dose based on body surface area).
Published reproduction studies with sodium picosulfate in pregnant rats and rabbits during the period of organogenesis did not show evidence of harm to the fetus at doses up to 100 mg/kg (approximately 49 and 98 times, respectively, the recommended human dose of 10 mg sodium picosulfate based on body surface area).

8.2 Lactation

Risk Summary
There are no data on the presence of magnesium oxide or anhydrous citric acid in either human or animal milk, the effects on the breastfed infant, or the effects on milk production. Published data on lactating women indicate that the active metabolite of sodium picosulfate, bis-(p-hydroxyphenyl)-pyridyl-2-methane (BHPM) remained below the limit of detection (1 ng/mL) in breast milk after both single and multiple doses of 10 mg/day. There are no data on the effects of sodium picosulfate on the breastfed infant or on milk production. The developmental and health benefits of breastfeeding should be considered along with the mother’s clinical need for sodium picosulfate, magnesium oxide and anhydrous citric acid and any potential adverse effects on the breastfed infant from sodium picosulfate, magnesium oxide and anhydrous citric acid or the underlying maternal condition.

8.4 Pediatric Use

The safety and effectiveness of sodium picosulfate, magnesium oxide and anhydrous citric acid have been established for cleansing of the colon as a preparation for colonoscopy in pediatric patients 9 years of age and older. Use of sodium picosulfate, magnesium oxide and anhydrous citric acid in this age group is supported by evidence from adequate and well-controlled trials of sodium picosulfate, magnesium oxide and anhydrous citric acid in adults and a single, dose-ranging, controlled trial in 78 pediatric patients 9 to 16 years of age [see Clinical Studies (14)]. The safety profile of sodium picosulfate, magnesium oxide and anhydrous citric acid in this pediatric population was similar to that seen in adults [see Adverse Reactions (6.1)]. Monitor for possible hypoglycemia in pediatric patients, as sodium picosulfate, magnesium oxide and anhydrous citric acid has no caloric substrate.
The safety and effectiveness of sodium picosulfate, magnesium oxide and anhydrous citric acid for oral solution in pediatric patients less than 9 years of age have not been established.

8.5 Geriatric Use

Of the 1,201 patients in clinical trials who received sodium picosulfate, magnesium oxide and anhydrous citric acid, 215 (18%) patients were 65 years of age or older. No overall differences in safety or effectiveness were observed between geriatric patients and younger patients. However, elderly patients are more likely to have decreased hepatic, renal or cardiac function and may be more susceptible to adverse reactions resulting from fluid and electrolyte abnormalities [see Warnings and Precautions (5.1)].

8.6 Renal Impairment

Sodium picosulfate, magnesium oxide and anhydrous citric acid is contraindicated in patients with severe renal impairment (creatinine clearance less than 30 mL/min), as accumulation of magnesium in plasma may occur [see Contraindications (4)]. Patients with mild to moderate renal impairment or patients taking concomitant medications that may affect renal function may be at increased risk for renal injury [see Warnings and Precautions (5.4)]. Advise these patients of the importance of adequate hydration before, during and after the use of sodium picosulfate, magnesium oxide and anhydrous citric acid [see Dosage and Administration (2.1)]. Consider performing baseline and post-colonoscopy laboratory tests (electrolytes, creatinine, and BUN) in these patients.

10 OVERDOSAGE

Overdosage of more than the recommended dose of sodium picosulfate, magnesium oxide and anhydrous citric acid may lead to severe electrolyte disturbances, as well as dehydration and hypovolemia, with signs and symptoms of these disturbances [see Warnings and Precautions (5.1)]. Monitor for fluid and electrolyte disturbances and treat symptomatically.

11 DESCRIPTION

Sodium picosulfate, magnesium oxide and anhydrous citric acid for oral solution is available in orange flavor, and is provided in two packets. The contents of each is to be dissolved in 5 ounces of cold water and consumed.
Each packet for orange flavor contains 10 mg sodium picosulfate, USP, 3.5 g magnesium oxide, USP and 12 g anhydrous citric acid, USP. The product also contains the following inactive ingredients: glyceryl behenate, orange flavor (contains dl-alpha-Tocopherol and Maize maltodextrin), potassium bicarbonate and saccharin sodium. The following is a description of the three active ingredients:
Sodium picosulfate is a stimulant laxative.
Sodium Picosulfate
• Chemical name: 4,4’-(2-Pyridylmethylene) diphenyl bis (hydrogen sulfate) disodium salt, monohydrate
• Chemical formula: C18H13NNa2O8S2.H2O
• Molecular weight: 499.4
• Structural formula:

• Sodium Picosulfate
Magnesium citrate, which is formed in solution by the combination of magnesium oxide and anhydrous citric acid, is an osmotic laxative.
Magnesium Oxide
• Chemical name: Magnesium oxide
• Chemical formula: Mg O
• Molecular weight: 40.3
• Structural formula: Mg O
Anhydrous Citric Acid
• Chemical name: 1,2,3-propanetricarboxylic acid, 2-hydroxy-
• Chemical formula: C6H8O7
• Molecular weight: 192.13
• Structural formula:

Anhydrous citric acid

12 CLINICAL PHARMACOLOGY

12.1 Mechanism of Action

Sodium picosulfate is hydrolyzed by colonic bacteria to form an active metabolite: bis-(p-hydroxy-phenyl)-pyridyl-2-methane, BHPM, which acts directly on the colonic mucosa to stimulate colonic peristalsis.
Magnesium oxide and citric acid react to create magnesium citrate in solution, which is an osmotic agent that causes water to be retained within the gastrointestinal tract.

12.2 Pharmacodynamics

The stimulant laxative activity of sodium picosulfate together with the osmotic laxative activity of magnesium citrate produces a purgative effect which, when ingested with additional fluids, produces watery diarrhea.

12.3 Pharmacokinetics

Absorption
After administration of the first packet of sodium picosulfate, magnesium oxide and anhydrous citric acid in 16 healthy subjects, mean maximum concentration (Cmax) for picosulfate of 2.3 ± 1.4 ng/mL was reached at 2 hours. After administration of 2 packets of sodium picosulfate, magnesium oxide and anhydrous citric acid separated by 6 hours, picosulfate reached the mean Cmax of 3.2 ± 2.6 ng/mL at approximately 7 hours (Tmax). In the same study, baseline uncorrected magnesium reached a Cmax of approximately 1.9 mEq/L, which occurred at 10 hours post first packet administration (Tmax). This represents an approximately 20% increase from the baseline.
Distribution
The apparent volume of distribution (V/F) for picosulfate was 4,199 liters in healthy adults.
Metabolism and Elimination
Sodium picosulfate, which is a prodrug, is converted to its active metabolite, BHPM, by colonic bacteria. Plasma concentration of the free BHPM were low, and below the lower limit of quantification (0.1 ng/mL) in 13 out of 16 subjects studied. The fraction of the sodium picosulfate dose excreted unchanged in urine was 0.2%. In urine, the majority of excreted BHPM was in the glucuronide- conjugated form. The terminal half-life of sodium picosulfate was 7.4 hours. The apparent clearance (CL/F) of picosulfate was 629 L/h.
Use in Specific Populations
Pediatric Patients
Pharmacokinetics of picosulfate was studied in pediatric patients aged from 9 to 16 years old.
For picosulfate, the apparent clearance is from 316 to 409 L/h. The corresponding estimates for apparent volume of distribution are from 2457 to 3935 liters. The derived half-life using these model estimates would be 7 hours. The picosulfate reached the mean Cmax of 3.5 ± 2.1 ng/mL at approximately 6 to 7 hours (Tmax)
The baseline uncorrected mean serum magnesium concentration was 2.02 mEq/L at 10 hours after the first dose of sodium picosulfate, magnesium oxide and anhydrous citric acid and ranged from 1.7 to 2.46 mEq/L in pediatric patients from 9 to 16 years of age.
Drug Interaction Studies
In an in vitro study using human liver microsomes, sodium picosulfate did not inhibit the major CYP enzymes (CYP 1A2, 2B6, 2C8, 2C9, 2C19, 2D6 and 3A4/5) evaluated. Based on an in vitro study using freshly isolated hepatocyte culture, sodium picosulfate is not an inducer of CYP1A2, CYP2B6 or CYP3A4/5.

13 NONCLINICAL TOXICOLOGY

13.1 Carcinogenesis, Mutagenesis, Impairment of Fertility

Long-term studies in animals to evaluate carcinogenic potential or studies to evaluate mutagenic potential have not been performed with sodium picosulfate, magnesium oxide and anhydrous citric acid. Sodium picosulfate was not mutagenic in the Ames test, the mouse lymphoma assay and the mouse bone marrow micronucleus test.
In an oral fertility study in rats, sodium picosulfate, magnesium oxide and anhydrous citric acid did not cause any significant adverse effect on male or female fertility parameters up to a maximum dose of 2,000 mg/kg twice daily (about 1.2 times the recommended human dose based on the body surface area).

14 CLINICAL STUDIES

Adults
The colon cleansing efficacy of sodium picosulfate, magnesium oxide and anhydrous citric acid was evaluated for non-inferiority against a comparator in two randomized, investigator-blinded, active-controlled, multicenter US trials in adult patients scheduled to have an elective colonoscopy. In all, 1,195 adult patients were included in the primary efficacy analysis: 601 from Study 1, and 594 from Study 2. Patients ranged in age from 18 to 80 years (mean age 56 years); 61% were female and 39% male. Self-identified race was distributed as follows: 90% White, 10% Black, and less than 1% other. Of these, 3% self-identified their ethnicity as Hispanic or Latino.
Patients randomized to sodium picosulfate, magnesium oxide and anhydrous citric acid in the two studies were treated with one of two dosing regimens:
• In Study 1, sodium picosulfate, magnesium oxide and anhydrous citric acid was given by “Split-Dose” (evening before and day of) dosing, where the first packet was taken the evening before the colonoscopy (between 5:00 and 9:00 PM), followed by five (5) 8-ounce glasses of clear liquid, and the second packet was taken the morning of the colonoscopy (at least 5 hours prior to but no more than 9 hours prior to colonoscopy), followed by three (3) 8-ounce glasses of clear liquid.
• In Study 2, sodium picosulfate, magnesium oxide and anhydrous citric acid was given by “Day-Before” (afternoon/evening before only) dosing, where both packets were taken separately on the day before the colonoscopy, with the first packet taken in the afternoon (between 4:00 and 6:00 PM), followed by five (5) 8-ounce glasses of clear liquid, and the second packet taken in the late evening (approximately 6 hours later, between 10:00 PM and 12:00 AM), followed by three (3) 8-ounce glasses of clear liquid.
The comparator was a preparation containing two liters of polyethylene glycol plus electrolytes solution (PEG + E) and two 5-mg bisacodyl tablets, administered the day before the procedure. All patients in both the sodium picosulfate, magnesium oxide and anhydrous citric acid and comparator groups were limited to a clear liquid diet on the day before the procedure (24 hours before).
The primary efficacy endpoint was the proportion of patients with successful colon cleansing, as assessed by blinded colonoscopists using the Aronchick Scale. The Aronchick scale is a tool used to assess overall colon cleansing. Successful colon cleansing was defined as bowel preparations with >90% of the mucosa seen and mostly liquid stool that were graded excellent (minimal suctioning needed for adequate visualization) or good (significant suctioning needed for adequate visualization) by the colonoscopist.
In both studies, sodium picosulfate, magnesium oxide and anhydrous citric acid was non-inferior to the comparator. In addition, sodium picosulfate, magnesium oxide and anhydrous citric acid provided by Split-Dose dosing met the pre-specified criteria for superiority to the comparator for colon cleansing in Study 1. The comparator in that study was administered entirely on the day prior to colonoscopy. See Tables 3 and 4 below.
Table 3: Proportion of Patients with Successful Colon Cleansing in Study 1 Split-Dose Regimen

Sodium picosulfate, magnesium oxide and anhydrous citric acid Split-Dose Regimen | 2 L PEG+E* with 2 x 5-mg bisacodyl tablets | Difference between treatment groups
% (n/N) | % (n/N) | Difference | 95% CI
84 % (256/304) | 74.4 % (221/297) | 10% | (3.4%, 16.2%)†

* 2L PEG + E = two liters polyethylene glycol plus electrolytes solution.
† Non-inferior and superior 2L PEG+E with 2 x 5 mg bisacodyl tablets
Table 4: Proportion of Patients with Successful Colon Cleansing in Study 2 Day-Before Regimen

Sodium picosulfate, magnesium oxide and anhydrous citric acid Day-Before Regimen | 2 L PEG+E* with 2 x 5mg bisacodyl tablets | Difference between treatment groups
% (n/N) | % (n/N) | Difference | 95% CI
83% (244/294) | 80% (239/300) | 3 % | (-2.9%, 9.6%)‡

* 2L PEG + E = two liters polyethylene glycol plus electrolytes solution.
‡ Non-inferior
Pediatric Patients 9 Years of Age and Older
Sodium picosulfate, magnesium oxide and anhydrous citric acid was evaluated for colon cleansing in a randomized, assessor-blind, multicenter, dose-ranging, active-controlled study in 78 pediatric patients 9 years to 16 years of age. The majority of patients were female (68%), white (91%), and of non-Hispanic or non-Latino ethnicity (95%). The mean age was 12 years of age. All 78 patients were included in the primary efficacy analysis.
Patients aged 9 years to 12 years were randomized into 3 arms (1:1:1):
• Sodium picosulfate, magnesium oxide and anhydrous citric acid one-half packet administered as two doses
• Sodium picosulfate, magnesium oxide and anhydrous citric acid one-packet administered as two doses
• comparator (oral PEG-based solution per local standard of care).
Patients aged 13 years to 16 years were randomized into 2 arms (1:1):
• Sodium picosulfate, magnesium oxide and anhydrous citric acid one-packet administered as two doses
• comparator (oral PEG-based solution per local standard of care)
Patients randomized to sodium picosulfate, magnesium oxide and anhydrous citric acid had two options for dosing, as determined by the investigator. The “Split Dose” regimen was the preferred method and the “Day Before” regimen was the alternative method if the “Split Dose” was not appropriate.
“Split-Dose” Regimen: (evening before and day of) dosing, where the first dose was taken the evening before the colonoscopy (between 5:00 and 9:00 PM), followed by five (5) 8-ounce glasses of clear liquid, and the second dose was taken the morning of the colonoscopy (at least 5 hours prior to but no more than 9 hours prior to colonoscopy), followed by three (3) 8-ounce glasses of clear liquid.
“Day-Before” Regimen: (afternoon/evening before only) dosing, where both doses were taken separately on the day before the colonoscopy, with the first dose taken in the afternoon (between 4:00 and 6:00 PM), followed by five (5) 8-ounce glasses of clear liquid, and the second dose taken in the late evening (approximately 6 hours later, between 10:00 PM and 12:00 AM), followed by three (3) 8-ounce glasses of clear liquid.
All patients randomized to sodium picosulfate, magnesium oxide and anhydrous citric acid were limited to a clear liquid diet on the day before the procedure. Those who received the comparator were given dietary instructions per the trial site’s standard of care.
The primary efficacy endpoint was the proportion of patients with successful colon cleansing as defined as a rating of either “Excellent” (> 90% of mucosa seen, mostly liquid stool, minimal suctioning needed for adequate visualization) or “Good” (> 90% of mucosa seen, mostly liquid stool, significant suctioning needed for adequate visualization) using the Aronchick scale, as assessed by blinded colonoscopists.
The sodium picosulfate, magnesium oxide and anhydrous citric acid regimen of one-half packet administered as two doses did not demonstrate comparable efficacy to the comparator, PEG, in patients 9 to 12 years of age and is not a recommended dosage regimen [see Dosage and Administration (2)].
The sodium picosulfate, magnesium oxide and anhydrous citric acid regimen of one packet administered as two doses demonstrated successful colon cleansing in both the 9 to 12 year age group and the 13 to 16 year age group. The efficacy rates were similar to those observed in the PEG groups, as shown in Table 5.
Table 5. Proportion of Patients 9 to 16 Years of Age with Successful Colon Cleansing^1

 | Sodium picosulfate, magnesium oxide and anhydrous citric acid One Packet Administered as Two Doses either as Split Dose or Day Before Regimen^2 |  | PEG Comparator^3
 | % (n/N) | 95% CI | % (n/N) | 95% CI
Age 9-12 | 88% (14/16) | (62, 98) | 81% (13/16) | (54, 96)
Age 13-16 | 81% (13/16) | (54, 96) | 86% (12/14) | (57, 98)

^1Successful colon cleansing as defined by “Excellent” or “Good” on the Aronchick scale
^2Of the 32 patients, 9 received the Split Dose Regimen and 23 the Day Before Regimen
^3Oral PEG-based preparation was used in the study as per standard of care

16 HOW SUPPLIED/STORAGE AND HANDLING

How Supplied
Sodium Picosulfate, Magnesium Oxide and Anhydrous Citric Acid for Oral Solution is supplied in a carton containing 2 packets, each holding 16.1 grams of powder in orange flavor, along with a pre-marked dosing cup. Each packet for orange flavor contains 10 mg of sodium picosulfate, 3.5 g of magnesium oxide and 12 g anhydrous citric acid. The excipients for orange flavor contains glyceryl behenate, orange flavor, potassium bicarbonate and saccharin sodium. The orange flavor contains dl-alpha-Tocopherol and maize maltodextrin.
Orange flavor:
Kit, 2 packets and cup NDC 31722-874-16
Storage
Store at 20º to 25ºC (68º to 77ºF) [see USP Controlled Room Temperature].

17 PATIENT COUNSELING INFORMATION

Advise the patient to read the FDA-approved patient labeling (Medication Guide and Instructions for Use).
Instruct patients:
• Each packet must be dissolved in 5 ounces of cold water and administered according to the dosing regimen. Direct ingestion of the undissolved powder may increase the risk of nausea, vomiting, dehydration, and electrolyte disturbances [see Warnings and Precautions (5.8)].
• Two doses (one packet per dose) of sodium picosulfate, magnesium oxide and anhydrous citric acid for oral solution are required for a complete preparation for colonoscopy either as a Split-Dose (preferred) or Day-Before dosing regimen.
• Not to take other laxatives while they are taking sodium picosulfate, magnesium oxide and anhydrous citric acid for oral solution.
• Do not eat solid food or dairy and do not drink anything colored red or purple.
• Do not drink alcohol.
• Do not take oral medications within one hour of starting sodium picosulfate, magnesium oxide and anhydrous citric acid for oral solution.
• If taking tetracycline or fluoroquinolone antibiotics, iron, digoxin, chlorpromazine, or penicillamine, take these medications at least 2 hours before and not less than 6 hours after administration of sodium picosulfate, magnesium oxide and anhydrous citric acid for oral solution.
• To follow the directions in the Instructions for Use, for either the Split-Dose or the Day-Before regimen, as prescribed.
• To consume additional fluids after each dose of sodium picosulfate, magnesium oxide and anhydrous citric acid for oral solution.
• To delay the second dose of sodium picosulfate, magnesium oxide and anhydrous citric acid for oral solution, if severe bloating, distention, or abdominal pain occurs following the first dose until the symptoms resolve.
• To contact their healthcare provider if they develop significant vomiting or signs of dehydration after taking sodium picosulfate, magnesium oxide and anhydrous citric acid for oral solution or if they experience altered consciousness (e.g. confusion, delirium, loss of consciousness) or seizures [see Warnings and Precautions (5.1, 5.3, 5.4)].

Manufactured for:
Camber Pharmaceuticals, Inc.
Piscataway, NJ 08854

By: Annora Pharma Pvt. Ltd.
Sangareddy - 502313, Telangana, India.

Revised: 08/2022

MEDICATION GUIDE

Sodium Picosulfate, Magnesium Oxide and Anhydrous Citric Acid for Oral Solution
(SOW dee um pye ko SUL fate, mag NEE zhum OKS ide & SI trik AS id)
Read and understand this Medication Guide and the Instructions for Use that come with sodium picosulfate, magnesium oxide and anhydrous citric acid for oral solution at least 2 days before your colonoscopy and again before you start taking sodium picosulfate, magnesium oxide and anhydrous citric acid for oral solution.
What is the most important information I should know about sodium picosulfate, magnesium oxide and anhydrous citric acid for oral solution?
Sodium picosulfate, magnesium oxide and anhydrous citric acid for oral solution and other bowel preparations can cause serious side effects, including:
Serious loss of body fluid (dehydration) and changes in blood salts (electrolytes) in your blood. These changes can cause:
• abnormal heartbeats that can cause death.
• seizures . This can happen even if you have never had a seizure.
• kidney problems.
Your chance of having fluid loss and changes in blood salts with sodium picosulfate, magnesium oxide and anhydrous citric acid for oral solution is higher if you:
• have heart problems
• have kidney problems
• take water pills or non-steroidal anti-inflammatory drugs (NSAIDS)
Tell your healthcare provider right away if you have any of these symptoms of a loss of too much body fluid (dehydration) while taking sodium picosulfate, magnesium oxide and anhydrous citric acid for oral solution:
• vomiting • dizziness
• urinating less often than normal • headache
See “What are the possible side effects of sodium picosulfate, magnesium oxide and anhydrous citric acid for oral solution?” for more information about side effects.
What is sodium picosulfate, magnesium oxide and anhydrous citric acid for oral solution?
Sodium picosulfate, magnesium oxide and anhydrous citric acid for oral solution is a prescription medicine used by adults and children 9 years of age and older, to clean the colon before a colonoscopy. Sodium picosulfate, magnesium oxide and anhydrous citric acid for oral solution cleans your colon by causing you to have diarrhea. Cleaning your colon helps your healthcare provider see the inside of your colon more clearly during your colonoscopy.
It is not known if sodium picosulfate, magnesium oxide and anhydrous citric acid for oral solution is safe and effective in children under 9 years of age.
Do not take sodium picosulfate, magnesium oxide and anhydrous citric acid for oral solution if your healthcare provider has told you that you have:
• serious kidney problems.
• a blockage in your intestine (bowel obstruction).
• an opening in the wall of your stomach or intestines (bowel perforation).
• a very dilated intestine (toxic megacolon).
• problems with the emptying of food and fluid from your stomach (gastric retention).
• an allergy to any of the ingredients in sodium picosulfate, magnesium oxide and anhydrous citric acid for oral solution. See the end of this Medication Guide for a complete list of ingredients in sodium picosulfate, magnesium oxide and anhydrous citric acid for oral solution.
Before taking sodium picosulfate, magnesium oxide and anhydrous citric acid for oral solution, tell your healthcare provider about all of your medical conditions, including if you:
• have problems with serious loss of body fluid (dehydration) and changes in blood salts (electrolytes).
• have a history of seizures or take medicines for seizures.
• are withdrawing from drinking alcohol or from taking benzodiazepines.
• have low blood salt (sodium) level.
• have kidney problems or take medicines for kidney problems.
• have heart problems.
• have stomach or bowel problems including ulcerative colitis.
• have problems with swallowing or gastric reflux.
• are pregnant. It is not known if sodium picosulfate, magnesium oxide and anhydrous citric acid for oral solution will harm your unborn baby. Talk to your healthcare provider if you are pregnant.
• are breastfeeding or plan to breastfeed. It is not known if sodium picosulfate, magnesium oxide and anhydrous citric acid passes into your breast milk. You and your healthcare provider should decide if you will take sodium picosulfate, magnesium oxide and anhydrous citric acid for oral solution while breastfeeding.
Tell your healthcare provider about all the medicines you take, including prescription and over-the-counter medicines, vitamins, and herbal supplements.
Sodium picosulfate, magnesium oxide and anhydrous citric acid for oral solution may affect how other medicines work, and other medicines may affect how sodium picosulfate, magnesium oxide and anhydrous citric acid for oral solution works. Medicines taken by mouth may not be absorbed properly when taken within 1 hour before the start of sodium picosulfate, magnesium oxide and anhydrous citric acid for oral solution.
Especially tell your healthcare provider if you take:
• medicines for blood pressure or heart problems.
• medicines for kidney problems.
• medicines for seizures.
• water pills (diuretics).
• nonsteroidal anti-inflammatory medicines (pain medicines).
• medicines for depression or mental health problems.
• laxatives. Do not take other laxatives while taking sodium picosulfate, magnesium oxide and anhydrous citric acid for oral solution.
The following medicines should be taken at least 2 hours before starting sodium picosulfate, magnesium oxide and anhydrous citric acid for oral solution and not less than 6 hours after taking sodium picosulfate, magnesium oxide and anhydrous citric acid for oral solution:
• tetracycline • digoxin (Lanoxin)
• fluoroquinolone antibiotics • chlorpromazine
• iron • penicillamine (Cuprimine, Depen)
Ask your healthcare provider or pharmacist for a list of these medicines if you are not sure if you are taking the medicines listed above.
Know the medicines you take. Keep a list of them to show your healthcare provider and pharmacist when you get a new medicine.
How should I take sodium picosulfate, magnesium oxide and anhydrous citric acid for oral solution?
See the Instructions for Use for dosing instructions. You must read, understand, and follow these instructions to take sodium picosulfate, magnesium oxide and anhydrous citric acid for oral solution the right way .
• Take sodium picosulfate, magnesium oxide and anhydrous citric acid for oral solution exactly as your healthcare provider tells you to take it.
• Do not take sodium picosulfate, magnesium oxide and anhydrous citric acid powder that has not been mixed with water. It may increase your risk of nausea, vomiting, and fluid loss (dehydration).
• Each packet of sodium picosulfate, magnesium oxide and anhydrous citric acid powder must be mixed with 5 ounces of cold water before drinking.
• It is important for you to drink the additional prescribed amount of clear liquids listed in the Instructions for Use to prevent fluid loss (dehydration).
• Two doses of sodium picosulfate, magnesium oxide and anhydrous citric acid for oral solution are required for a complete colonoscopy preparation. 1 packet of sodium picosulfate, magnesium oxide and anhydrous citric acid for oral solution equals 1 dose.
• There are 2 different methods for taking sodium picosulfate, magnesium oxide and anhydrous citric acid for oral solution. It is better (preferred) to use the Split-Dose method. If you cannot do the Split-Dose method, you can take sodium picosulfate, magnesium oxide and anhydrous citric acid for oral solution using the Day-Before method. See the Instructions for Use for more information.
• All people taking sodium picosulfate, magnesium oxide and anhydrous citric acid for oral solution should follow these general instructions starting 1 day before your colonoscopy:
o only drink clear liquids all day and the next day until 2 hours before your colonoscopy. Stop drinking all fluids at least 2 hours before the colonoscopy.
o after taking sodium picosulfate, magnesium oxide and anhydrous citric acid for oral solution if you have any bloating or feeling like your stomach is upset, wait to take your second dose until your stomach feels better.
• While taking sodium picosulfate, magnesium oxide and anhydrous citric acid for oral solution, do not:
o take any other laxatives.
o take any medicines by mouth (oral) within 1 hour of starting sodium picosulfate, magnesium oxide and anhydrous citric acid for oral solution.
o eat solid foods, dairy such as milk, or alcohol while taking sodium picosulfate, magnesium oxide and anhydrous citric acid for oral solution and until after your colonoscopy.
o eat or drink anything colored red or purple.
Contact your healthcare provider right away if after taking sodium picosulfate, magnesium oxide and anhydrous citric acid for oral solution you have severe vomiting, signs of dehydration, changes in consciousness such as feeling confused, delirious or fainting (loss of consciousness) or seizures after taking sodium picosulfate, magnesium oxide and anhydrous citric acid for oral solution.
What are the possible side effects of sodium picosulfate, magnesium oxide and anhydrous citric acid for oral solution?
Sodium picosulfate, magnesium oxide and anhydrous citric acid for oral solution can cause serious side effects, including:
• See “What is the most important information I should know about sodium picosulfate, magnesium oxide and anhydrous citric acid for oral solution?”
• Changes in certain blood tests. Your healthcare provider may do blood tests after you take sodium picosulfate, magnesium oxide and anhydrous citric acid for oral solution to check your blood for changes. Tell your healthcare provider if you have any symptoms of too much fluid loss, including:
o vomiting
o nausea
o bloating
o dizziness
o stomach-area (abdomen) cramping
o urinate less than usual
o trouble drinking clear liquids
o trouble swallowing
o seizures
o heart problems
• Ulcers of the bowel or bowel problems (ischemic colitis). Tell your healthcare provider right away if you have severe stomach-area (abdomen) pain or rectal bleeding.
The most common side effects of sodium picosulfate, magnesium oxide and anhydrous citric acid for oral solution in adults include:
• nausea • headache • vomiting
The most common side effects of sodium picosulfate, magnesium oxide and anhydrous citric acid for oral solution in children 9 to 16 years of age include:
• nausea • vomiting • stomach area (abdominal) pain
These are not all the possible side effects of sodium picosulfate, magnesium oxide and anhydrous citric acid for oral solution.
Call your doctor for medical advice about side effects. You may report side effects to FDA at 1-800-FDA-1088.
How should I store sodium picosulfate, magnesium oxide and anhydrous citric acid for oral solution?
• Store sodium picosulfate, magnesium oxide and anhydrous citric acid for oral solution at room temperature between 68ºF to 77ºF (20ºC to 25ºC).
Keep sodium picosulfate, magnesium oxide and anhydrous citric acid for oral solution and all medicines out of the reach of children.
General information about the safe and effective use of sodium picosulfate, magnesium oxide and anhydrous citric acid for oral solution.
Medicines are sometimes prescribed for purposes other than those listed in a Medication Guide. Do not use sodium picosulfate, magnesium oxide and anhydrous citric acid for oral solution for a condition for which it was not prescribed. Do not give sodium picosulfate, magnesium oxide and anhydrous citric acid for oral solution to other people, even if they are going to have the same procedure you are. It may harm them. You can ask your pharmacist or healthcare provider for information about sodium picosulfate, magnesium oxide and anhydrous citric acid for oral solution that is written for health professionals.
What are the ingredients in sodium picosulfate, magnesium oxide and anhydrous citric acid for oral solution?
Sodium picosulfate, magnesium oxide and anhydrous citric acid for oral solution comes in a carton containing 2 packets, each containing 16.1 grams of powder in orange flavor, along with a pre-marked dosing cup.
Active ingredients: sodium picosulfate, magnesium oxide and anhydrous citric acid
Inactive ingredients: glyceryl behenate, orange flavor (contains dl-alpha-Tocopherol and Maize maltodextrin), potassium bicarbonate and saccharin sodium.
For more information, call Annora Pharma Private Limited at 1-866-495-1995.
This Medication Guide has been approved by the U.S. Food and Drug Administration

Medication guide available at http://camberpharma.com/medication-guides

Manufactured for:
Camber Pharmaceuticals, Inc.,
Piscataway, NJ 08854

By: Annora Pharma Pvt. Ltd.
Sangareddy - 502313, Telangana, India.

Revised: 08/2022
INSTRUCTIONS FOR USE
Sodium Picosulfate, Magnesium Oxide and Anhydrous Citric Acid for Oral Solution
(SOW dee um pye ko SUL fate, mag NEE zhum OKS ide & SI trik AS id)
Before Taking sodium picosulfate, magnesium oxide and anhydrous citric acid for oral solution
There are 2 different methods for taking sodium picosulfate, magnesium oxide and anhydrous citric acid for oral solution. It is better (preferred) to use the Split-Dose method. If you cannot use the Split-Dose method, you can take sodium picosulfate, magnesium oxide and anhydrous citric acid for oral solution using the Day-Before method. Talk with your healthcare provider before you start if you have any questions.
• Start a clear-liquid diet theday before your colonoscopy. Only drink clear liquids all day the day before your colonoscopy, and the next day until 2 hours before your colonoscopy. Stop drinking all fluids at least 2 hours before the colonoscopy.
• You must drink enough clear liquids to keep your body hydrated for the entire day before your colonoscopy.
Important:
See Table 1 for a list of liquids you can drink for your clear liquid diet.

Table 1: List of liquids for the clear-liquid diet

- Water (plain or flavored)
- Black coffee or tea (no milk, cream, soy, or nondairy creamer)
- Clear broth or bouillon
- Sports drinks (not red or purple)
- Clear juices without pulp (such as apple juice or white grape juice)
- Ginger ale and other sodas (not red or purple)
- Plain jello (not red or purple)
- Frozen juice bars (not red or purple)

Important:
See Table 2 for the items you cannot eat or drink before your colonoscopy.

Table 2: Do not eat or drink these items during the clear-liquid diet

- no solid foods
- no alcohol
- no dairy or non-dairy types of milk or cream
- no soy milk or drinks
- no juices with pulp
- no red or purple drinks
- no other liquids that you cannot see through

Important:
• Sodium picosulfate, magnesium oxide and anhydrous citric acid is a powder that must be added to cold water right before use.
• Do not prepare the solution ahead of time. Take sodium picosulfate, magnesium oxide and anhydrous citric acid for oral solution right after it is prepared.
• Do not swallow the powder without adding it to cold water first.
Split-Dose Instructions
Dose 1 – In the evening the day before your colonoscopy (sometime between 5:00 PM to 9:00 PM)
• Fill the dosing cup with cold water up to the lower line (5 ounces).
Note: Do not use any other clear liquid to mix sodium picosulfate, magnesium oxide and anhydrous citric acid for oral solution.

• Open 1 packet of sodium picosulfate, magnesium oxide and anhydrous citric acid and add all of the powder to the cold water in the dosing cup. To open the sodium picosulfate, magnesium oxide and anhydrous citric acid packet cut along the dotted line at the top of the packet using scissors.
• Stir for 2 to 3 minutes to dissolve the powder. Use a clock or timer The dosing cup may feel slightly warm as the powder dissolves. This is normal.
• Drink all the solution right away.
Note: Sodium picosulfate, magnesium oxide and anhydrous citric acid powder should be mixed in cold water immediately before use. Do not prepare the solution ahead of time or store the solution for later use. Do not refrigerate or add ice to the solution.
• Follow this sodium picosulfate, magnesium oxide and anhydrous citric acid for oral solution dose by drinking at least five 8 ounce cups of clear liquid (using the upper line on the dosing cup provided- see figure below) over the next 5 hours.

• After taking sodium picosulfate, magnesium oxide and anhydrous citric acid for oral solution if you have any bloating or feeling like your stomach is upset, wait to take your second dose until your stomach feels better.
Important: See Table 1 for a list of acceptable clear liquids.
Dose 2 - In the morning of colonoscopy (approximately 5 hours prior to colonoscopy)
Note: Do not eat solid food. Drink only clear liquids.
• Fill the dosing cup with cold water up to the lower line (5 ounces).
Note: Do not use any other clear liquid to mix sodium picosulfate, magnesium oxide and anhydrous citric acid for oral solution.

• Open the second packet of sodium picosulfate, magnesium oxide and anhydrous citric acid and add all the powder to the cold water in the dosing cup.
• Stir for 2 to 3 minutes to dissolve the powder. Use a clock or timer.
• Drink all the solution right away.
Note: Sodium picosulfate, magnesium oxide and anhydrous citric acid powder should be mixed in cold water immediately before use. Do not prepare the solution ahead of time or store the solution for later use. Do not refrigerate or add ice to the solution.
• Follow this sodium picosulfate, magnesium oxide and anhydrous citric acid for oral solution dose by drinking at least three 8 ounce cups of clear liquids (using the upper line on the dosing cup -see figure below). You can continue to drink clear liquids up to 2 hours before the colonoscopy.

Important: See Table 1 for a list of acceptable clear liquids.
Stop drinking clear liquids 2 hours before your colonoscopy, or as advised by your healthcare provider.
Day-Before Instructions
Dose 1 – In the afternoon or early evening the day before your colonoscopy (sometime between 4:00 PM to 6:00 PM)
• Fill the dosing cup with cold water up to the lower line (5 ounces).
Note: Do not use any other clear liquid to mix sodium picosulfate, magnesium oxide and anhydrous citric acid for oral solution.

• Open 1 packet of sodium picosulfate, magnesium oxide and anhydrous citric acid and add all the powder to the cold water in the dosing cup. To open the sodium picosulfate, magnesium oxide and anhydrous citric acid packet cut along the dotted line at the top of the packet using scissors.
• Stir for 2 to 3 minutes to dissolve the powder. Use a clock or timer. The dosing cup may feel slightly warm as the powder dissolves. This is normal.
• Drink all the solution right away.
Note: Sodium picosulfate, magnesium oxide and anhydrous citric acid powder should be mixed in cold water immediately before use. Do not prepare the solution ahead of time or store the solution for later use. Do not refrigerate or add ice to the solution.
• Follow this sodium picosulfate, magnesium oxide and anhydrous citric acid for oral solution dose by drinking at least five 8 ounce cups of clear liquids (using the upper line on the dosing cup -see figure below) over the next 5 hours.

After taking sodium picosulfate, magnesium oxide and anhydrous citric acid for oral solution if you have any bloating or feeling like your stomach is upset, wait to take your second dose until your stomach feels better.
Important: See Table 1 for a list of acceptable clear liquids.
Dose 2 – In the evening before your colonoscopy (sometime between 10:00 PM to 12:00 AM):
Note: Do not eat solid food. Drink only clear liquids.

• Fill the dosing cup with cold water up to the lower line (5 ounces).
Note: Do not use any other clear liquid to mix sodium picosulfate, magnesium oxide and anhydrous citric acid for oral solution.
• Open the second packet of sodium picosulfate, magnesium oxide and anhydrous citric acid and add all of the powder to the cold water in the dosing cup. Stir for 2 to 3 minutes to dissolve the powder. Use a clock or timer.
• Drink all of this solution right away.
Note: Sodium picosulfate, magnesium oxide and anhydrous citric acid powder should be mixed in cold water immediately before use. Do not prepare the solution ahead of time or store the solution for later use. Do not refrigerate or add ice to the solution.
• Follow this sodium picosulfate, magnesium oxide and anhydrous citric acid for oral solution dose by drinking at least three 8 ounce cups of clear liquids (using the upper line on the dosing cup -see figure below) over the next 5 hours.

Important: See Table 1 for a list of acceptable clear liquids.
Stop drinking clear liquids 2 hours before your colonoscopy, or as advised by your healthcare provider.
This Instructions for Use has been approved by the U.S. Food and Drug Administration.

Revised: 08/2022

PACKAGE LABEL.PRINCIPAL DISPLAY PANEL

Sodium Picosulfate, Mgo and Anhydrous Citric Acid Container Carton Label

Sodium Picosulfate, Mgo and Anhydrous Citric Acid Sachet Label